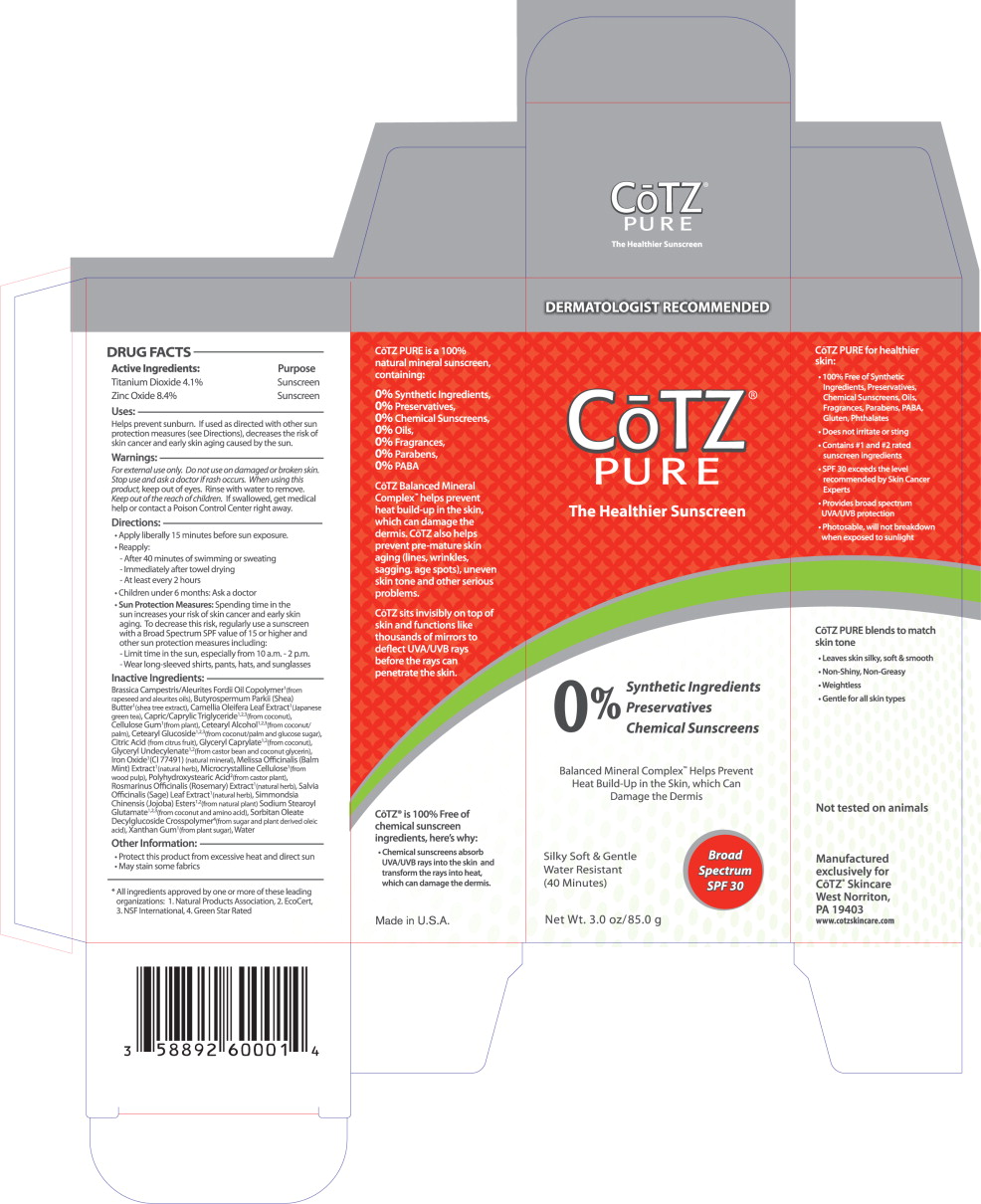 DRUG LABEL: Cotz Pure SPF 30 
NDC: 58892-600 | Form: CREAM
Manufacturer: Fallien Cosmeceuticals, LTD.
Category: otc | Type: HUMAN OTC DRUG LABEL
Date: 20121218

ACTIVE INGREDIENTS: Titanium Dioxide 41 mg/1 g; Zinc Oxide 84 mg/1 g
INACTIVE INGREDIENTS: Shea Butter; Camellia Oleifera Leaf; Medium-Chain Triglycerides; Carboxymethylcellulose Sodium; Cetostearyl Alcohol; Cetearyl Glucoside; Anhydrous Citric Acid; Glyceryl Caprylate; Ferric Oxide Red; Melissa Officinalis; Cellulose, Microcrystalline; Polyhydroxystearic Acid (2300 MW); Rosemary; Sage; Sodium Stearoyl Glutamate; Xanthan Gum; Water

DRUG FACTS

Active Ingredients:

Titanium Dioxide 4.1%

Zinc Oxide 8.4%

Purpose

Sunscreen

Sunscreen

Uses:

Helps prevent sunburn. If used as directed with other sun protection measures (see Directions), decreases the risk of skin cancer and early skin aging caused by the sun.

Warnings:

For external use only.

Do not use on damaged or broken skin.

Stop use and ask a doctor if rash occurs.

When using this product, keep out of eyes. Rinse with water to remove.

KEEP OUT OF REACH OF CHILDREN

Keep out of the reach of children. If swallowed, get medical help or contact a Poison Control Center right away.

Directions:

- Apply liberally 15 minutes before sun exposure.
- Reapply:
  - After 40 minutes of swimming or sweating
  - Immediately after towel drying
  - At least every 2 hours
- Children under 6 months: Ask a doctor
- Sun Protection Measures: Spending time in the sun increases your risk of skin cancer and early skin aging. To decrease this risk, regularly use a sunscreen with a Broad Spectrum SPF value of 15 or higher and other sun protection measures including:
  - Limit time in the sun, especially from 10 a.m. - 2 p.m.
  - Wear long-sleeved shirts, pants, hats, and sunglasses

Inactive Ingredients:

Brassica Campestris/Aleurites Fordii Oil Copolymer^1 (from rapeseed and aleurites oils), Butyrospermum Parkii (Shea) Butter^1 (shea tree extract), Camellia Oleifera Leaf Extract^1 (Japanese green tea), Capric/Caprylic Triglyceride^1,2,3(from coconut), Cellulose Gum1(from plant), Cetearyl Alcohol^1,2,3(from coconut/ palm), Cetearyl Glucoside^1,2,3(from coconut/palm and glucose sugar), Citric Acid (from citrus fruit), Glyceryl Caprylate^1,2(from coconut), Glyceryl Undecylenate^1,2(from castor bean and coconut glycerin), Iron Oxide^1 (CI 77491) (natural mineral), Melissa Officinalis (Balm Mint) Extract^1 (natural herb), Microcrystalline Cellulose^1 (from wood pulp), Polyhydroxystearic Acid^2(from castor plant), Rosmarinus Officinalis (Rosemary) Extract^1 (natural herb), Salvia Officinalis (Sage) Leaf Extract^1 (natural herb), Simmondsia Chinensis (Jojoba) Esters^1,2(from natural plant) Sodium Stearoyl Glutamate^1,2,3(from coconut and amino acid), Sorbitan Oleate Decylglucoside Crosspolymer^4(from sugar and plant derived oleic acid), Xanthan Gum^1(from plant sugar), Water

Other Information:

- Protect this product from excessive heat and direct sun
- May stain some fabrics

* All ingredients approved by one or more of these leading organizations: 1. Natural Products Association, 2. EcoCert, 3 NSF International, 4. Green Star Rated

Principal Display Panel – SPF 30 85g Carton Label

DERMATOLOGIST RECOMMENDED

CoTZ®

PURE

The Healthier Sunscreen
0%
Synthetic Ingredients
Preservatives
Chemical Sunscreens

Balanced Mineral ComplexTM Helps Prevent
Heat Build-Up in Skin, which Can
Damage the Dermis

Broad
Spectrum
SPF 30

Silky Soft & Gentle
Water Resistant
(40 minutes)

Net Wt. 3.5 oz/85.0 g